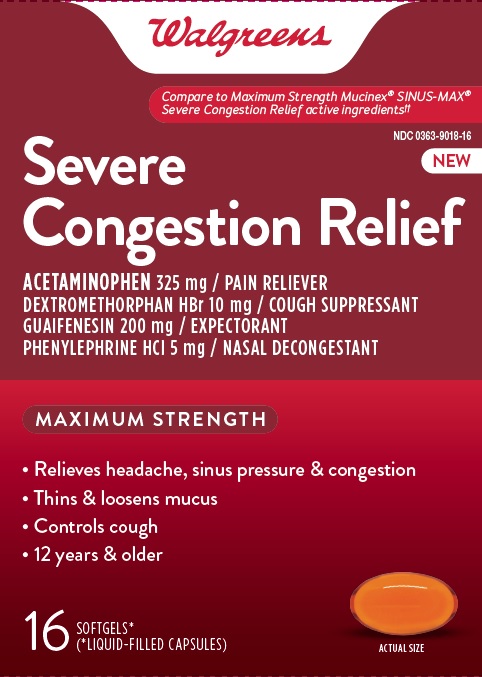 DRUG LABEL: Severe Congestion Relief
NDC: 0363-9018 | Form: CAPSULE, LIQUID FILLED
Manufacturer: Walgreens
Category: otc | Type: HUMAN OTC DRUG LABEL
Date: 20260119

ACTIVE INGREDIENTS: ACETAMINOPHEN 325 mg/1 1; GUAIFENESIN 200 mg/1 1; DEXTROMETHORPHAN HYDROBROMIDE 10 mg/1 1; PHENYLEPHRINE HYDROCHLORIDE 5 mg/1 1
INACTIVE INGREDIENTS: FD&C YELLOW NO. 6; GELATIN; GLYCERIN; POLYETHYLENE GLYCOL 400; POVIDONE K30; PROPYLENE GLYCOL; WATER; SORBITOL; SORBITAN; TITANIUM DIOXIDE

WALGREENS Severe Congestion Relief

Drug Facts

ACTIVE INGREDIENT

Active ingredients (in each softgel) | Purpose
Acetaminophen 325 mg | Pain reliever/fever reducer
Dextromethorphan HBr 10 mg | Cough suppressant
Guaifenesin 200 mg | Expectorant
Phenylephrine HCl 5 mg | Nasal decongestant

Uses

- temporarily relieves:
- nasal congestion
- headache
- minor aches and pains
- sinus congestion and pressure
- cough
- temporarily promotes nasal and/or sinus drainage
- helps loosen phlegm (mucus) and thin bronchial
  secretions to rid the bronchial passageways of
  bothersome mucus and make coughs more
  productive.

Warnings

Liver warning

This product contains acetaminophen. Severe liver damage may occur if you take

- more than 12 softgels in 24 hours, which is the maximum daily amount
- with other drugs containing acetaminophen
- 3 or more alcoholic drinks every day while using this product

Allergy Alert

Acetaminophen may cause severe skin reactions. Symptoms may include:

- skin reddening
- blisters
- rash

If a skin reaction occurs, stop use and seek medical help right away.

Do not use

- with any other drug containing acetaminophen (prescription or nonprescription). If you are not sure whether a drug contains acetaminophen ask a doctor or pharmacist.
- if you are now taking a prescription monoamine oxidase inhibitor (MAOI) (certain drugs for depression, psychiatric or emotional conditions, or Parkinson's disease), or for 2 weeks after stopping the MAOI drug. If you do not know if your prescription drug contains an MAOI, ask a doctor or pharmacist before taking this product.

Ask a doctor before use if you have

- liver disease
- heart disease
- high blood pressure
- thyroid disease
- diabetes
- trouble urinating due to enlarged prostate gland
- cough that occurs with too much phlegm (mucus)
- persistent or chronic cough such as occurs with smoking, asthma, chronic bronchitis, or emphysema

Ask a doctor or pharmacist before use if you are taking the blood thinning drug warfarin.

When using this product, do not use more than directed.

Stop use and ask a doctor if

- nervousness, dizziness, or sleeplessness occur
- pain, nasal congestion, or cough gets worse or lasts more than 7 days
- fever gets worse or lasts more than 3 days
- redness or swelling is present
- new symptoms occur
- cough comes back or occurs with rash or headache that lasts

These could be signs of a serious condition.

PREGNANCY OR BREAST FEEDING

If pregnant or breast-feeding, ask a health professional before use.

Keep out of reach of children.

Overdose warning

Taking more than directed can cause serious health problems. In case of overdose, get medical help or contact a Poison Control Center right away. Quick medical attention is critical for adults as well as for children even if you do not notice any signs or symptoms.

Directions

- do not take more than directed - see Overdose warning
- do not take more than 12 softgels in any 24 hour period
- adults & children 12 years & over : take 2 softgels every 4 hours
- children under 12 years of age: do not use

Other information

- store at 20-25^0C (68-77^0F)
- avoid excessive heat

Inactive ingredients

FD&C Yellow # 6, gelatin,
glycerin, polyethylene glycol, povidone, propylene
glycol, purified water, sorbitol sorbitan , titanium
dioxide

Questions or comments?

1-888-333-9792